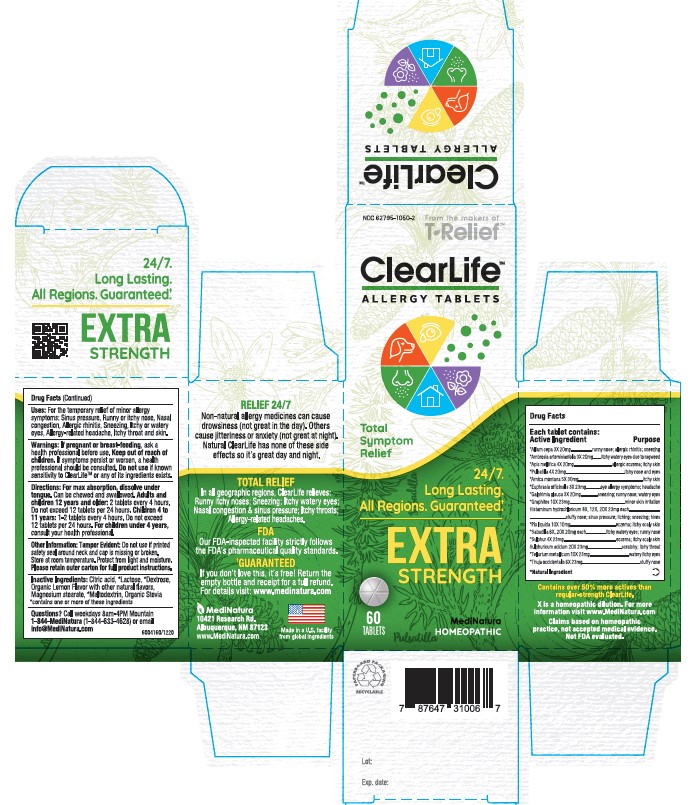 DRUG LABEL: Clearlife Extra Strength
NDC: 62795-1050 | Form: TABLET
Manufacturer: MediNatura Inc.
Category: homeopathic | Type: HUMAN OTC DRUG LABEL
Date: 20230605

ACTIVE INGREDIENTS: ONION 3 [hp_X]/1 1; AMBROSIA ARTEMISIIFOLIA WHOLE 3 [hp_X]/1 1; APIS MELLIFERA 4 [hp_X]/1 1; ARNICA MONTANA 5 [hp_X]/1 1; EUPHRASIA STRICTA 3 [hp_X]/1 1; GRAPHITE 10 [hp_X]/1 1; GALPHIMIA GLAUCA FLOWERING TOP 3 [hp_X]/1 1; PULSATILLA VULGARIS WHOLE 4 [hp_X]/1 1; HISTAMINE DIHYDROCHLORIDE 8 [hp_X]/1 1; PINE TAR 10 [hp_X]/1 1; SCHOENOCAULON OFFICINALE SEED 6 [hp_X]/1 1; SULFUR 4 [hp_X]/1 1; SULFURIC ACID 20 [hp_X]/1 1; TELLURIUM 10 [hp_X]/1 1; THUJA OCCIDENTALIS LEAFY TWIG 6 [hp_X]/1 1
INACTIVE INGREDIENTS: CITRIC ACID MONOHYDRATE; LACTOSE, UNSPECIFIED FORM; MAGNESIUM STEARATE; STEVIA REBAUDIUNA LEAF; DEXTROSE; MALTODEXTRIN

Clearlife Extra Strength

• KEEP OUT OF REACH OF CHILDREN

• INDICATIONS AND USAGE

For the temporary relief of minor allergy symptoms:
Sinus Pressure, runny or itchy nose, Nasal congestion,
Allergic Rhinitis, Sneezing, itchy or watery eyes, Allergy related headache, Itchy throat and skin.

• WARNINGS

If pregnant or breast-feeding, ask a healthcare provider before use. Keep out of reach of children. If symptoms persist or worsen, a health professional should be consulted. Do not use if known sensitivity to ClearLife™ or any of its ingredients exists.

Directions

For max absorption dissolve under tongue. Can be chewed and swallowed.
Adults and children 12 years and older: 2 tablets every 4 hours. Do not exceed 12 tablets in 24 hours
Children 4 to 11 years: 1-2 tablets every 4 hours. Do not exceed 12 tablets in 24 hours
For Children under 4 years, consult your health professional.

• ACTIVE INGREDIENTS

Active Ingredients: Each tablet contains: *Allium Cepa 3X 20 mg *Ambrosia Artmemisiaefolia 3X 20 mg *Apis Mellfica 4X 20 mg. *Pulsatilla 4X 20 mg. *Arnica montana, 5X 30 mg,*Euphrasia officinalis 3X 23 mg, *Graphites10X 23 mg *Galphimia glauca 3X 20 mg, *Histaminum hydrochloricum 8X, 12X, 20X, 23 mg. each, *Pix liquida 10X 10 mg * Sabadilla 6X 20X 20 mg each, *Sulphur 4X 23 mg, *Sulphuricum acidum 20X 23 mg, *Tellurium metallicum 10X 23 mg, *Thuja occidentalis 6X 23 mg.

• INACTIVE INGREDIENT

Citric Acid, Lactose, Dextrose, Organic Lemon flavors with other natural flavors, Magnesium stearate, Maltodextrin, Organic Stevia. Contains one or more of these ingredients.

• PURPOSE

• Sinus Pressure, runny, stuffy or itchy nose, Nasal congestion,
• Allergic Rhinitis, Sneezing, allergic eczema, itchy or watery eyes, Allergy related headache, Itchy throat and skin.

PACKAGE LABEL

Add image transcription here...